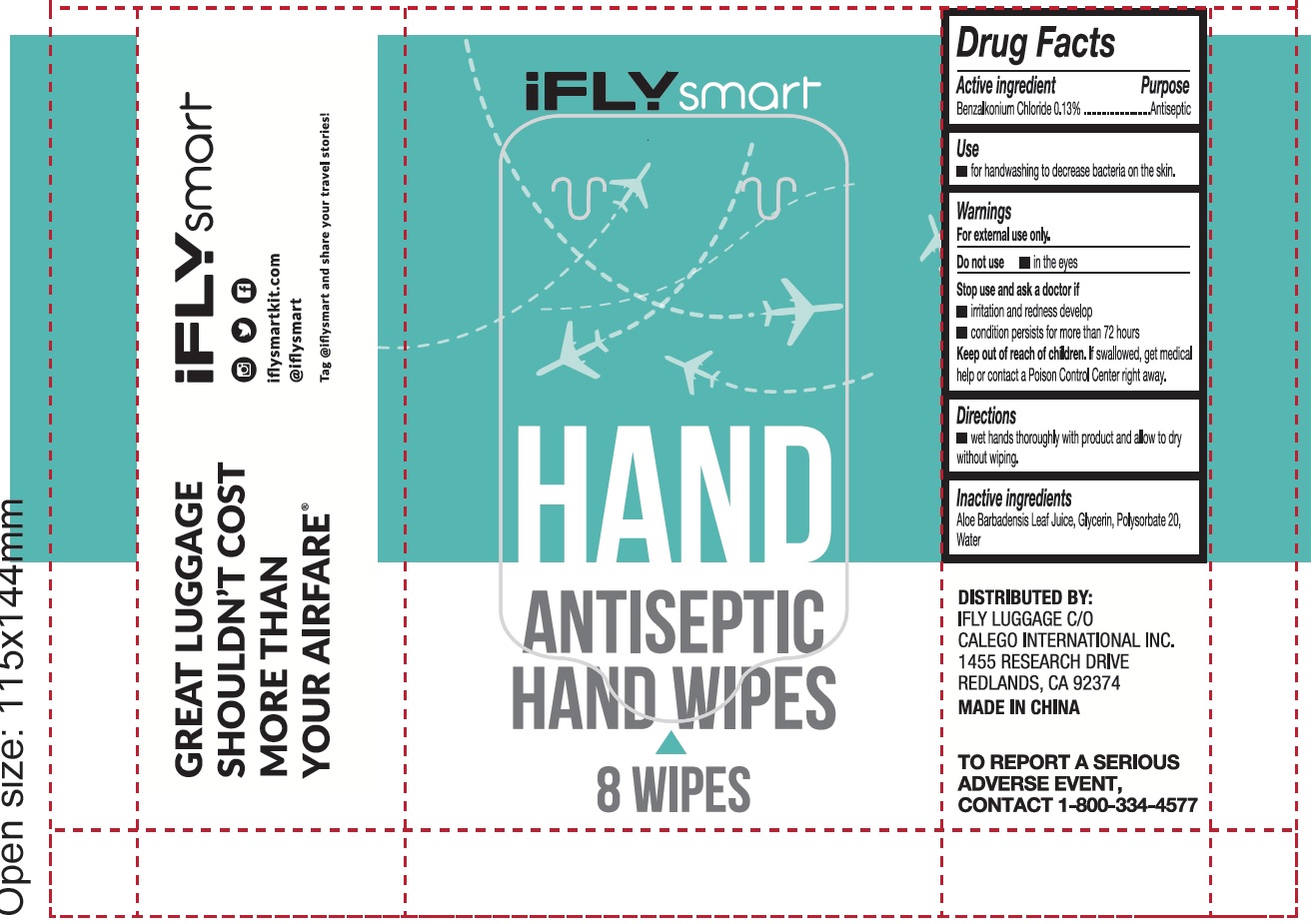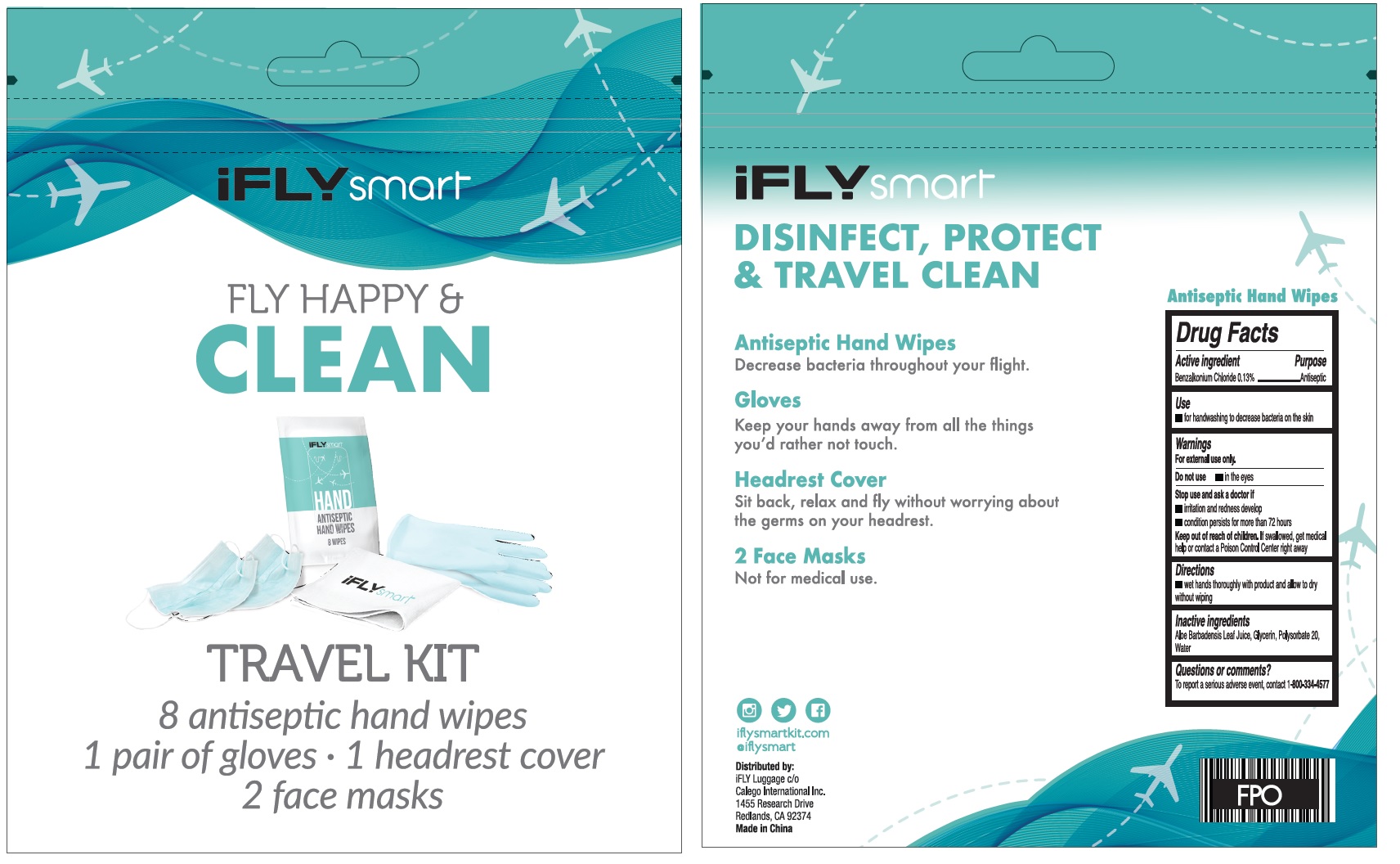 DRUG LABEL: iFLYSmart Fly Happy And Clean Kit
NDC: 72487-004 | Form: KIT | Route: TOPICAL
Manufacturer: Calego International Inc
Category: otc | Type: HUMAN OTC DRUG LABEL
Date: 20200921

ACTIVE INGREDIENTS: BENZALKONIUM CHLORIDE 0.13 g/100 g
INACTIVE INGREDIENTS: ALOE VERA LEAF; GLYCERIN; POLYSORBATE 20; WATER

iFLYSmart Fly Happy & Clean Kit

Active ingredient

Benzalkonium Chloride 0.13%

Purpose

Antiseptic

Use

- for handwashing to decrease bacteria on the skin

Warnings

For external use only.

Do not use

- in the eyes

Stop use and ask a doctor if

- irritation and redness develop
- condition persists for more than 72 hours

Keep out of reach of children.

If swallowed, get medical help or contact a Poison Control Center right away

Directions

- wet hands thoroughly with product and allow to dry without wiping

Inactive ingredients

Aloe Barbadensis Leaf Juice, Glycerin, Polysorbate 20, Water

QUESTIONS

TO REPORT A SERIOUS ADVERSE EVENT, CONTACT 1-800-334-4577